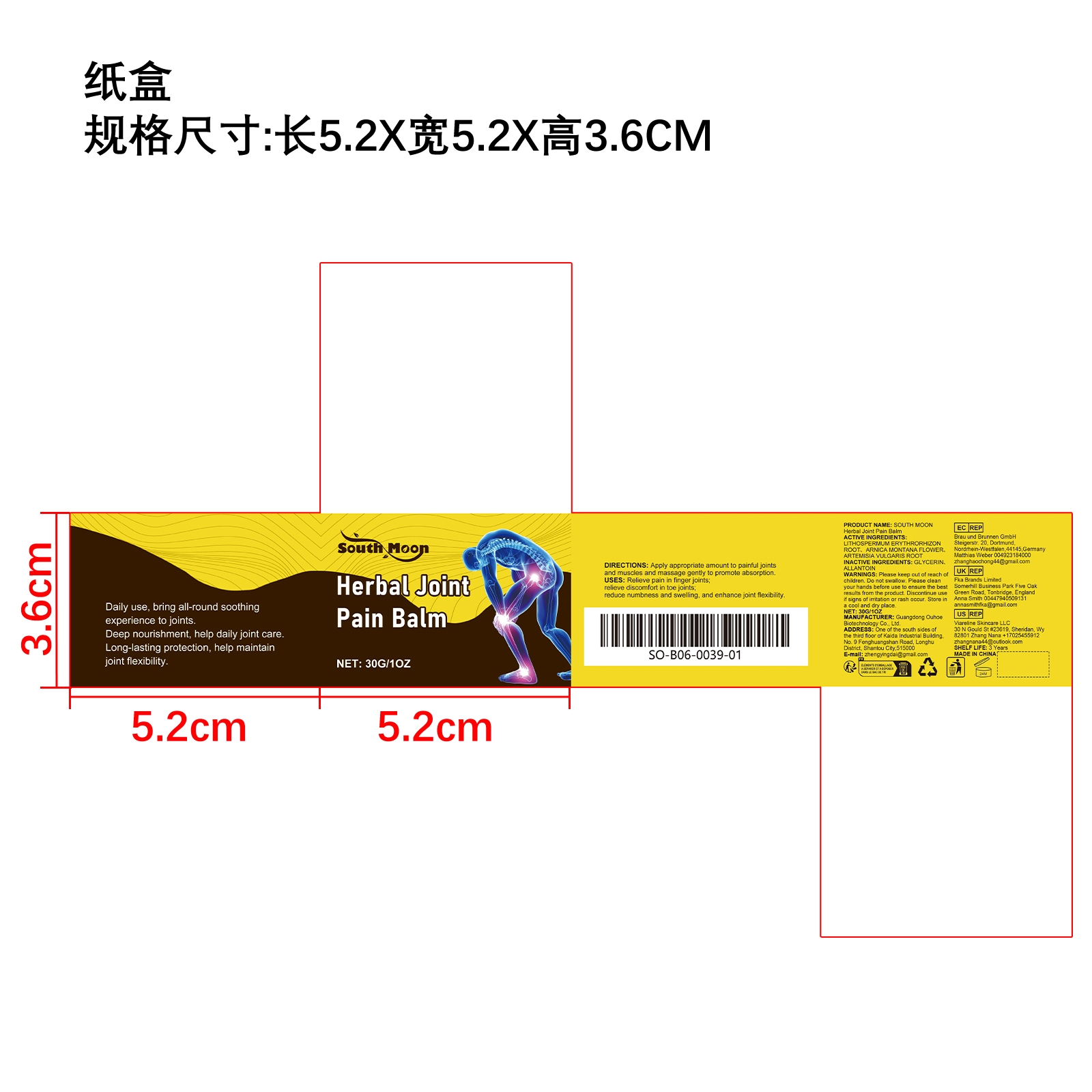 DRUG LABEL: SOUTH MOON Herbal Joint Pain Balm
NDC: 84744-071 | Form: CREAM
Manufacturer: Guangdong Ouhoe Biotechnology Co., Ltd.
Category: otc | Type: HUMAN OTC DRUG LABEL
Date: 20241101

ACTIVE INGREDIENTS: LITHOSPERMUM ERYTHRORHIZON ROOT 9 g/30 g; ARTEMISIA VULGARIS ROOT 4.5 g/30 g; ARNICA MONTANA FLOWER 3 g/30 g
INACTIVE INGREDIENTS: ALLANTOIN 9 g/30 g; GLYCERIN 4.5 g/30 g

ACTIVE INGREDIENTS

LITHOSPERMUM ERYTHRORHIZON ROOT,ARNICA MONTANA FLOWER,ARTEMISIA VULGARIS ROOT

purpose

Relieve pain in finger joints;relieve discomfort in toe joints;reduce numbness and swelling, and enhance joint flexibility.

uses

Apply appropriate amount to painful ioints and muscles and massage gently to promote absorption.

WARNINGS

Please keep out of reach of children. Do not swallow. Please clean your hands before use to ensure the best results from the product. Discontinue use if signs of irritation or rash occur. Store in a cool and dry place.

stop use

Discontinue use if signs of irritation or rash occur.

Do not use

Discontinue use if signs of irritation or rash occur.

KEEP OUT OF REACH OF CHILDREN

Please keep out of reach of children. Do not swallow.

STORAGE AND HANDLING

Store in a cool and dry place.

INACTIVE INGREDIENT

GLYCERIN、ALLANTOIN